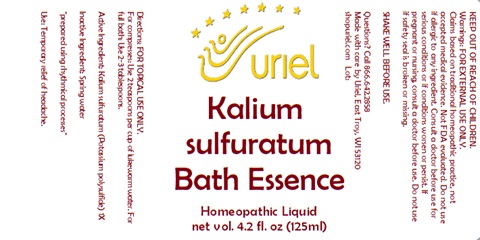 DRUG LABEL: Kalium Sulfuratum Bath Essence
NDC: 48951-6071 | Form: LIQUID
Manufacturer: Uriel Pharmacy Inc.
Category: homeopathic | Type: HUMAN OTC DRUG LABEL
Date: 20240131

ACTIVE INGREDIENTS: SULFUR 1 [hp_X]/1 mL
INACTIVE INGREDIENTS: WATER

Kalium Sulfuratum Bath Essence

INDICATIONS AND USAGE

Directions: FOR TOPICAL USE ONLY.

DOSAGE AND ADMINISTRATION

For compresses: Use 2 teaspoons per cup of lukewarm water. For full bath: Use 2-3 tablespoons.

SHAKE WELL BEFORE USE.

Active Ingredient: Kalium sulfuratum (Potassium polysulfide) 1X

Inactive Ingredient: Spring water

"prepared using rhythmical processes"

PURPOSE

Use: Temporary relief of headache.

KEEP OUT OF REACH OF CHILDREN.

Warnings: FOR EXTERNAL USE ONLY.
Claims based on traditional homeopathic practice, not accepted medical evidence. Not FDA evaluated. Do not use if allergic to any ingredient. Consult a doctor before use for serious conditions or if conditions worsen or persist. If pregnant or nursing, consult a doctor before use. Do not use if safety seal is broken or missing.

Questions? Call 866.642.2858
Made with care by Uriel, East Troy, WI 53120
shopuriel.com Lot: